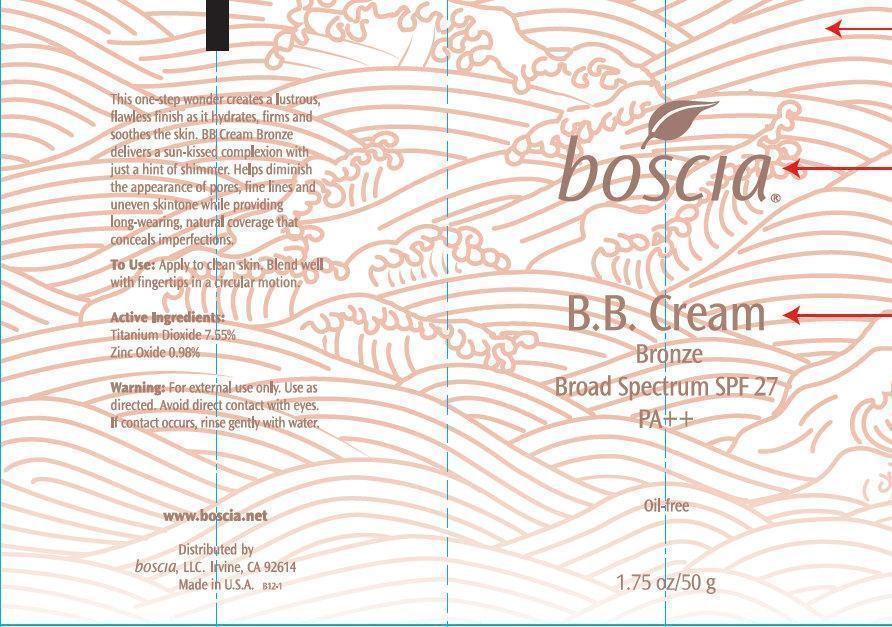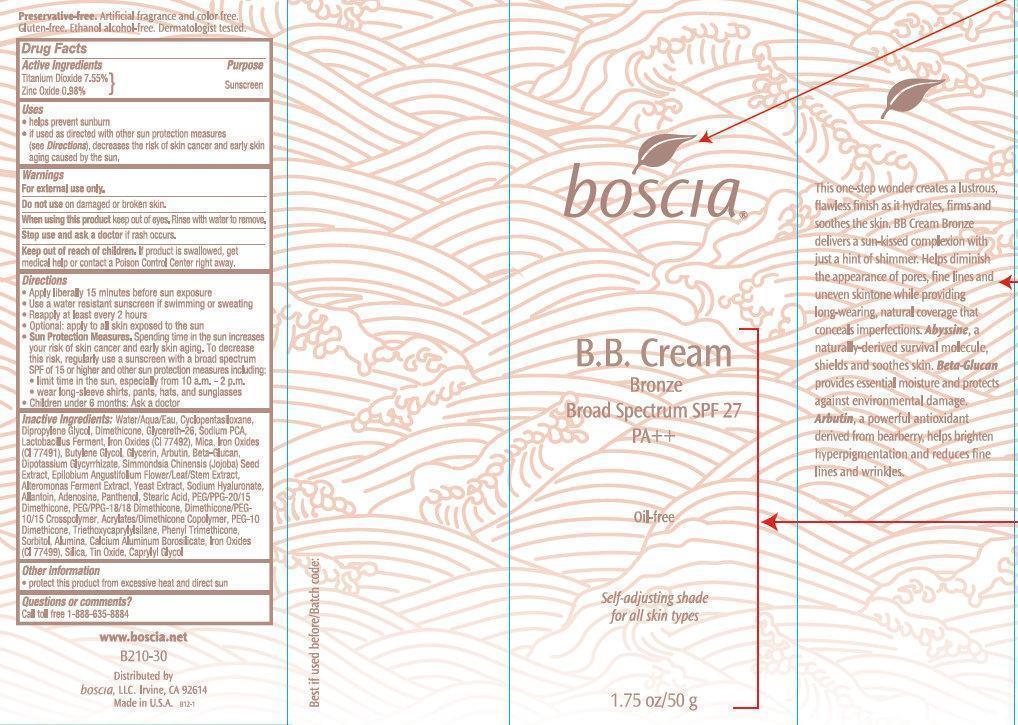 DRUG LABEL: Boscia BB BRONZE Broad Spectrum SPF 27 PA Self-Adjusting Shade
NDC: 76151-221 | Form: CREAM
Manufacturer: Boscia LLC
Category: otc | Type: HUMAN OTC DRUG LABEL
Date: 20231212

ACTIVE INGREDIENTS: TITANIUM DIOXIDE 7.55 g/100 g; ZINC OXIDE 0.98 g/100 g
INACTIVE INGREDIENTS: YEAST; HYALURONATE SODIUM; ALLANTOIN; PANTHENOL; STEARIC ACID; PEG/PPG-20/15 DIMETHICONE; PEG/PPG-18/18 DIMETHICONE; TRIETHOXYCAPRYLYLSILANE; SORBITOL; ALUMINUM OXIDE; CALCIUM ALUMINUM BOROSILICATE; FERROSOFERRIC OXIDE; SILICON DIOXIDE; STANNIC OXIDE; CAPRYLYL GLYCOL; WATER; CYCLOMETHICONE 5; DIPROPYLENE GLYCOL; DIMETHICONE; GLYCERETH-26; SODIUM PYRROLIDONE CARBOXYLATE; FERRIC OXIDE YELLOW; MICA; FERRIC OXIDE RED; BUTYLENE GLYCOL; GLYCERIN; ARBUTIN; GLYCYRRHIZINATE DIPOTASSIUM; SIMMONDSIA CHINENSIS SEED; EPILOBIUM ANGUSTIFOLIUM FLOWERING TOP

Boscia BB Cream BRONZE Broad Spectrum SPF 27 PA Oil-Free Self-Adjusting Shade

Active Ingredients

Titanium Dioxide 7.55%

Zinc Oxide 0.98%

Purpose

Sunscreen

Uses

- helps prevent sunburn

- if used as directed with other sun protection measures (see), decreases the risk of skin cancer and early skin aging caused by the sun. Directions

Warnings

For external use only.

Do not use

on damaged or broken skin.

When using this product

keep out of eyes, Rinse with water to remove.

Stop use and ask a doctor

if rash occurs.

keep out of reach of children

If product is swallowed, get medical help or contact a Poison Control Center right away.

Directions

- Apply liberally 15 minutes before sun exposure
- Use a water resistance sunscreen if swimming or sweating
- Reapply at least every 2 hours
- Optional: apply to all skin exposed to the sun.

- , Spending time in the sun increases your risk cancer and early skin aging. To decrease this risk, regularly use a sunscreen with a broad spectrum SPF of 15 or higher and other sun protection measures including: Sun Protection Measures

- limit time in the sun, especially from 10 a.m. - 2 p.m.
- wear long-sleeve shirts, pants, hats, and sunglasses
- Children under 6 months: Ask a doctor

Inactive Ingredients

Water/Aqua/Eau, Cyclopentasiloxane, Dipropylene Glycol, Dimethicone, Glycereth-26, Sodium PCA, Lactobacillus Ferment, Iron Oxides (CI 77492), Mica, Iron Oxides (CI 77491), Butylene Glycol, Glycerin, Arbutin, Beta-Glucan, Dipotassium Glycyrrhizate, Simmondsia Chinensis (Jojoba) Seed Extract, Epilobium Angustifolium Flower/Leaf/Stem Extract, Alteromonas Ferment Extract, Yeast Extract, Sodium Hyaluronate, Allantoin, Adenosine, Panthenol, Stearic Acid, PEG/PPG-20/15 Dimethicone, PEG/PPG-18/18 Dimethicone, Dimethicone/PEG-10/15 Crosspolymer, Acrylates/Dimethicone Copolymer, PEG-10 Dimethicone, Triethoxycaprylylsilane, Phenyl Trimethicone, Sorbitol, Alumina, Calcium Aluminum Borosilicate, Iron Oxides (CI 77499), Silica, Tin Oxide, Caprylyl Glycol.

Other information

- protect this product from excessive heat and direct sun

Questions or comments?

Call toll free 1-888-635-8884

boscia B.B Cream Bronze

This one-step wonder creates a lustrous, flawless finish as it hydrates, firms and soothes the skin. BB cream Bronze delivers a sun-kissed complexion with just a hint of shimmer. Helps diminish the appearances of pores, fine lines and uneven skintone while providing long-wearing, natural coverage that conceals imperfections, , a naturally-derived survival mollecule, shields and soothes skin. provides essential moisture and protects against environmental damage. a powerful antioxidant derived from bearberry, helps brighten hyperpigmentation and reduces fine lines and wrinkles. Abyssine Beta-Glucan Arbutin,

. Artificial fragrance and color free. Gluten-free, Ethanol alcohol-free. Dermatologist tested. Preservative-free

PACKAGE LABEL

boscia B.B. Cream Bronze Broad Spectrum SPF 27 PA++ Oil-free Self-adjusting shade for all skin types 1.75 oz/ 50 g